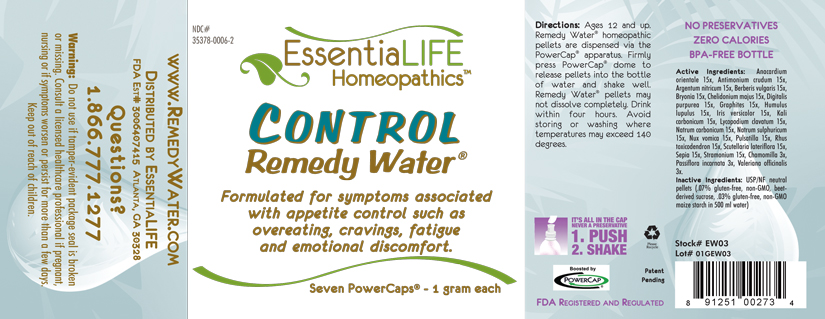 DRUG LABEL: Control Remedy Water 
NDC: 35378-0006 | Form: SOLUTION
Manufacturer: Georgetown Health, LLC DBA EssentiaLife
Category: homeopathic | Type: HUMAN OTC DRUG LABEL
Date: 20120610

ACTIVE INGREDIENTS: Semecarpus Anacardium Juice 15 [hp_X]/1 mg; Antimony Trisulfide 15 [hp_X]/1 mg; Silver Nitrate 15 [hp_X]/1 mg; Berberis Vulgaris Root Bark 15 [hp_X]/1 mg; Bryonia Alba Root 15 [hp_X]/1 mg; Chelidonium Majus 15 [hp_X]/1 mg; Digitalis 15 [hp_X]/1 mg; Graphite 15 [hp_X]/1 mg; Hops 15 [hp_X]/1 mg; Iris Versicolor Root 15 [hp_X]/1 mg; Potassium Carbonate 15 [hp_X]/1 mg; Lycopodium Clavatum Spore 15 [hp_X]/1 mg; Sodium Carbonate 15 [hp_X]/1 mg; Sodium Sulfate 15 [hp_X]/1 mg; Strychnos Nux-vomica Seed 15 [hp_X]/1 mg; Pulsatilla Vulgaris 15 [hp_X]/1 mg; Toxicodendron Pubescens Leaf 15 [hp_X]/1 mg; Scutellaria Lateriflora 15 [hp_X]/1 mg; Sepia Officinalis Juice 15 [hp_X]/1 mg; Datura Stramonium 15 [hp_X]/1 mg; Matricaria Recutita 3 [hp_X]/1 mg; Passiflora Incarnata Flower 3 [hp_X]/1 mg; Valerian 3 [hp_X]/1 mg
INACTIVE INGREDIENTS: Starch, Corn; Sucrose

Control Remedy Water®

Active Ingredients

Anacardium orientale | 15x
Antimonium crudum | 15x
Argentum nitricum | 15x
Berberis vulgaris | 15x
Bryonia | 15x
Chelidonium majus | 15x
Digitalis purpurea | 15x
Graphites | 15x
Humulus lupulus | 15x
Iris versicolor | 15x
Kali carbonicum | 15x
Lycopodium clavatum | 15x
Natrum carbonicum | 15x
Natrum sulphuricum | 15x
Nux vomica | 15x
Pulsatilla | 15x
Rhus toxicodendron | 15x
Scutellaria laterifolia | 15x
Sepia | 15x
Stramonium | 15x
Chamomilla | 3x
Passiflora incarnata | 3x
Valeriana officinalis | 3x

Purpose

Formulated for symptoms associated with appetite control such as overeating, cravings, fatigue and emotional discomfort.

Uses

Formulated for symptoms associated with appetite control such as overeating, cravings, fatigue and emotional discomfort.

Warnings

Do not use if tamper-evident package seal is broken or missing. Consult a licensed healthcare professional if pregnant, nursing or if symptoms worsen or persist for more than a few days. Keep out of reach of children.

Directions

Ages 12 and up. Remedy Water® homepathic pellets are dispersed via the PowerCap® apparatus. Firmly press PowerCap® dome to release pellets into the bottle of water and shake well. Remedy Water® pellets may not dissolve completely. Drink within four hours. Avoid storing or washing where temperatures may exceed 140 degrees.

Inactive Ingredients

USP/NF neutral pellets (.07% gluten-free, non-GMO, beet-derived sucrose, .03% gluten-free, non-GMO maize starch in 500 ml water)

Other Information

Avoid storing in areas where temperatures may exceed 140 degrees.

Questions?

1.866.777.1277
www.RemedyWater.com

PRINCIPAL DISPLAY PANEL

NDC# 35378-0006-2
EssentiaLIFE Homeopathics™
CONTROL Remedy Water®
Formulated for symptoms associated with appetite control such as overeating, cravings, fatigue and emotional discomfort.

Seven PowerCaps® - 1 gram each

Directions: Ages 12 and up. Remedy Water® homepathic pellets are dispersed via the PowerCap® apparatus. Firmly press PowerCap® dome to release pellets into the bottle of water and shake well. Remedy Water® pellets may not dissolve completely. Drink within four hours. Avoid storing or washing where temperatures may exceed 140 degrees.

IT'S ALL IN THE CAP
NEVER A PRESERVATIVE
1. PUSH
2. SHAKE

Please Recyle

Patent Pending

Boosted by PowerCap®

FDA Registered and Regulated

NO PRESERVATIVES
ZERO CALORIES
BPA-FREE BOTTLE

Active Ingredients: Anacardium orientale 15x, Antimonium crudum 15x, Argentum nitricum 15x, Berberis vulgaris 15x, Bryonia 15x, Chelidonium majus 15x,Digitalis purpurea 15x, Graphites 15x, Humulus lupulus 15x, Iris versicolor 15x, Kali carbonicum 15x, Lycopodium clavatum 15x, Natrum carbonicum 15x, Natrum sulphuricum 15x, Nux vomica 15x, Pulsatilla 15x, Rhus toxicodendron 15x, Scutellaria lateriflora 15x, Sepia 15x, Stramonium 15x, Chamomilla 3x, Passiflora incarnate 3x, Valeriana officinalis 3x.

Inactive ingredients: USP/NF neutral pellets (.07% gluten-free, non-GMO, beet-derived sucrose, .03% gluten-free, non-GMO maize starch in 500 ml water)

Stock# EW03

Lot# 01GEW03

www.RemedyWater.com

Distributed by EssentiaLIFE

FDA Est.# 3006407415 Atlanta, GA 30328

Questions?
1.866.777.1277

Warning: Do not use if tamper-evident package seal is broken or missing. Consult a licensed healthcare professional if pregnant, nursing or if symptoms worsen or persist for more than a few days. Keep out of reach of children.